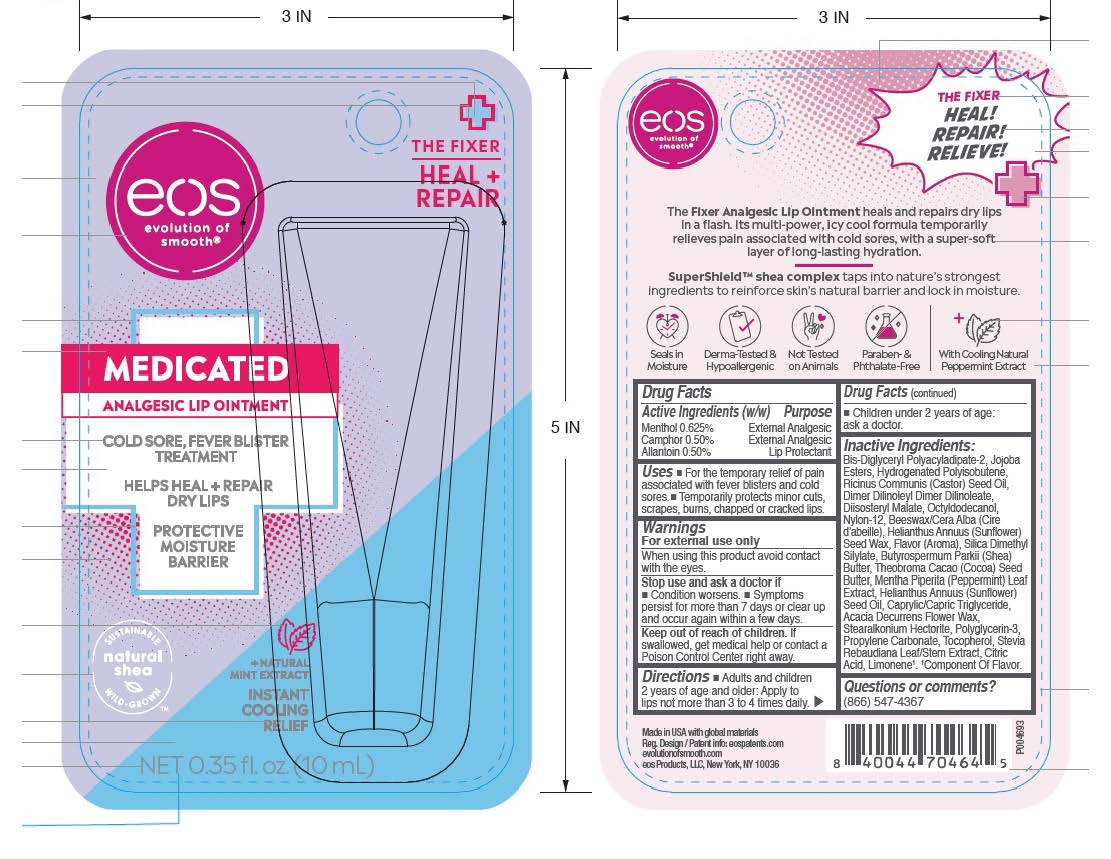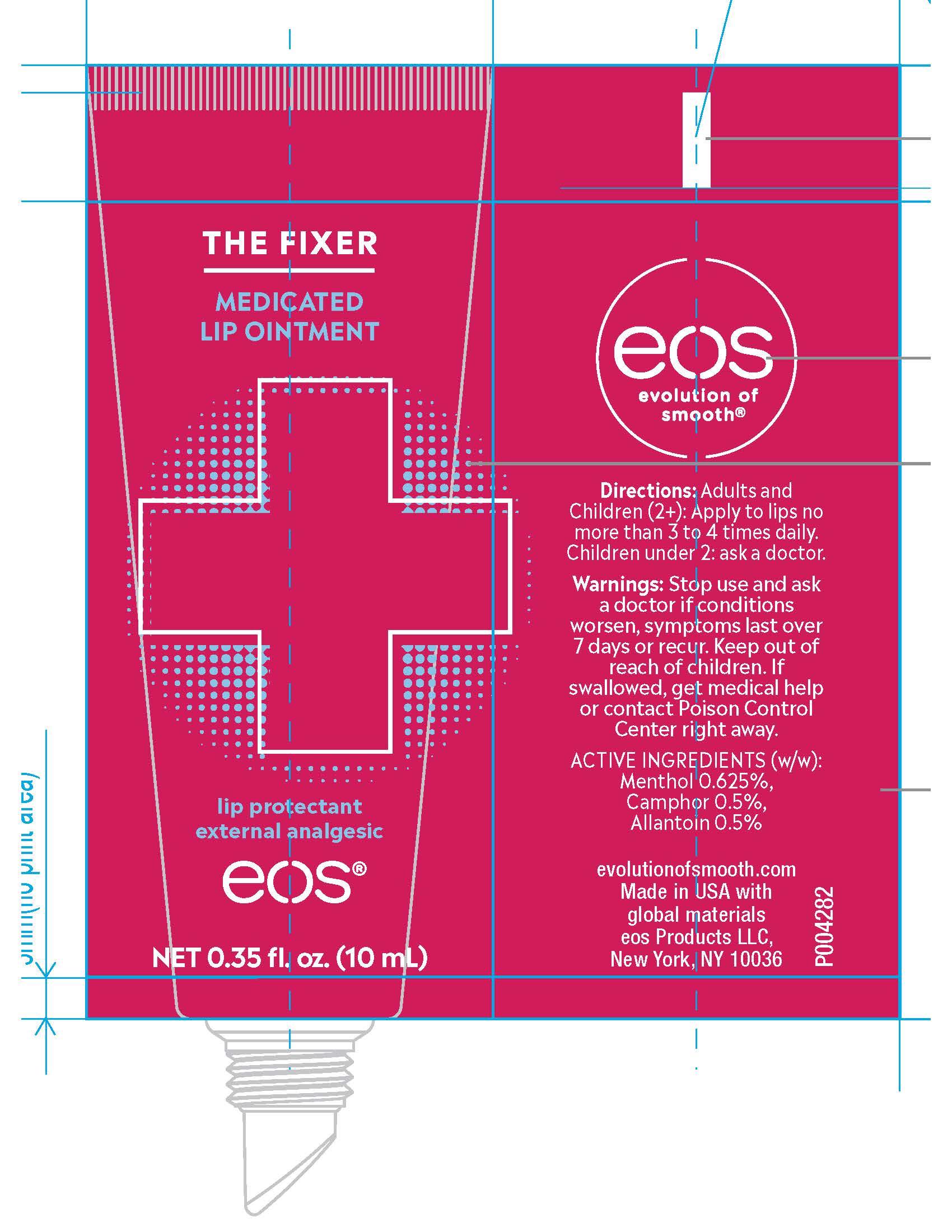 DRUG LABEL: eos THE FIXER HEAL REPAIR MEDICATED ANALGESIC LIP
NDC: 70170-0017 | Form: OINTMENT
Manufacturer: eos Products LLC
Category: otc | Type: HUMAN OTC DRUG LABEL
Date: 20241030

ACTIVE INGREDIENTS: MENTHOL 0.0594 g/10 mL; CAMPHOR (NATURAL) 0.0475 g/10 mL; ALLANTOIN 0.0475 g/10 mL
INACTIVE INGREDIENTS: HYDROLYZED JOJOBA ESTERS (ACID FORM); HELIANTHUS ANNUUS SEED WAX; ACACIA DECURRENS FLOWER WAX; POLYGLYCERIN-3; YELLOW WAX; BIS-DIGLYCERYL POLYACYLADIPATE-2; CASTOR OIL; OCTYLDODECANOL; SILICA DIMETHYL SILYLATE; MEDIUM-CHAIN TRIGLYCERIDES; STEARALKONIUM HECTORITE; PROPYLENE CARBONATE; COCOA BUTTER; SHEA BUTTER; HYDROGENATED POLYBUTENE (1300 MW); DIISOSTEARYL MALATE; DIMER DILINOLEYL DIMER DILINOLEATE; NYLON-12; SUNFLOWER OIL; MENTHA PIPERITA LEAF; CITRIC ACID MONOHYDRATE; LIMONENE, (+)-; TOCOPHEROL; STEVIA REBAUDIUNA LEAF

eos THE FIXER HEAL REPAIR MEDICATED ANALGESIC LIP

Drug Facts

Active ingredients Purpose

Menthol 0.625% External Analgesic

Camphor 0.50% External Analgesic

Allantoin 0.50% Lip Protectant

Uses

- For the temporary relief of pain associated with fever blisters and cold sores.
- Temporarily protect minor cuts, scrapes, burns, chapped or cracked lips.

Warnings

For external use only.

When using this productavoid contact with eyes.

Stop use and ask a doctor if

- Condition worsens.
- Symptoms persist for more than 7 days or clear up and occur again within a few days.

Keep out of reach of children.If swallowed, get medical help or contact a Poison Control Centre right away.

Directions

- Adults and children 2 years of age and older: Apply to lips not more than 3 to 4 times daily.
- Children under 2 years of age: ask a doctor.

Inactive Ingredients:

Bis-Diglyceryl Polyacyladipate-2, Jojoba Esters, Hydrogenated Polyisobutene, Ricinus Communis (Castor) Seed Oil, Dimer Dilinoleyl Dimer Dilinoleate, Diiosteryl Malate, Octyldodecanol, Nylon-12, Beeswax/Cera Alba (Cire d'abeille), Helianthus Annuus (Sunflower) Seed Wax, Flavor (Armoa), Silica Dimethyl Silylate, Butyrospermum Parkii (Shea) Butter, Theoborma Cacao (Cocoa) Seed Butter, Mentha Piperita (Peppermint) Leaf Extract, Helianthus Annuus (Sunflower) Seed Oil, Caprylic/Capric Triglyceride, Acacia Decurrens Flower Wax, Stearalkonium Hectorite, Polyglycerin-3, Propylene Carbonate, Tocopherol, Stevia Rebaudiana Leaf/Stem Extract, Citric Acid, Limonene^1.^1Component of Flavor.

Questions or comments?

(866) 547-4367

Principal Display Pantel - 0.35 fl. oz. (10 mL)

eos

THE FIXER

HEAL + REPAIR

MEDICATED

ANALGESIC LIP OINTMENT

COLD SORE, FEVER BLISTER TREATMENT

HELPS HEAL + REPAIR DRY LIPS

PROTECTIVE MOISTURE BARRIER

+NATURAL MINT EXTRACT

INSTANT COOLING RELIEF

NET 0.35 fl. oz. (10 mL)